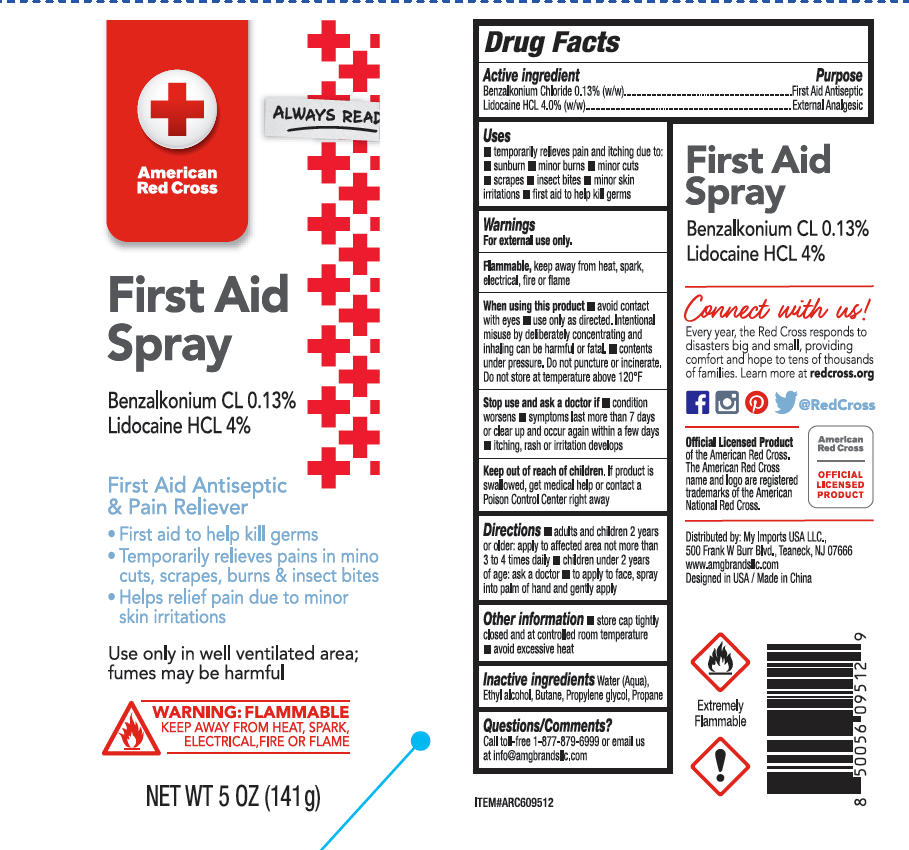 DRUG LABEL: American Red Cross First Aid
NDC: 51628-4529 | Form: SPRAY
Manufacturer: MY IMPORTS USA LLC
Category: otc | Type: HUMAN OTC DRUG LABEL
Date: 20251027

ACTIVE INGREDIENTS: LIDOCAINE HCL 4 g/100 g; BENZALKONIUM CHLORIDE 0.13 g/100 g
INACTIVE INGREDIENTS: PROPANE; WATER; BUTANE; ALCOHOL; PROPYLENE GLYCOL

American Red Cross First Aid Spray

Active ingredients

Benzalkonium Chloride 0.13%(w/w)

Lidocaine HCL 4.0%(w/w)

Purpose

First Aid Antiseptic

External Analgesic

Uses

- temporarily relieves pain and itching due to: sunburn, minor burns, minor cuts, scrapes, insect bites, minor skin irritations, first aid to help kill germs.

Warnings

For external use only.

Flammable, keep away from heat, spark, electrical, fire or flame.

When using this product

- avoid contact with eyes
- use only as directed. Intentional misuse by deliberately concentrating and inhaling can be harmful or fatal.
- contents under pressure. Do not puncture or incinerate. Do not store at temperature above 120ºF.

Stop use and ask a doctor if

- condition worsens
- symptoms last more than 7 days or clear up and occur again within a few days
- itching, rash or irritation develops

Keep out of reach out children

If product is swallowed, get medical help or contact a Poison Control Center right away

Directions

- adult and children 2 years or older: apply to affected area not more than 3 to 4 times daily
- children under 2 years of age: ask a doctor
- to apply to face, spray into palm of hand and gently apply

Other information

- Store cap tightly closed and at controlled room temperature
- avoid excessive heat

Inactive ingredients

Water(Aqua)

Butane

Ethyl alcohol

Propylene glycol

Propane